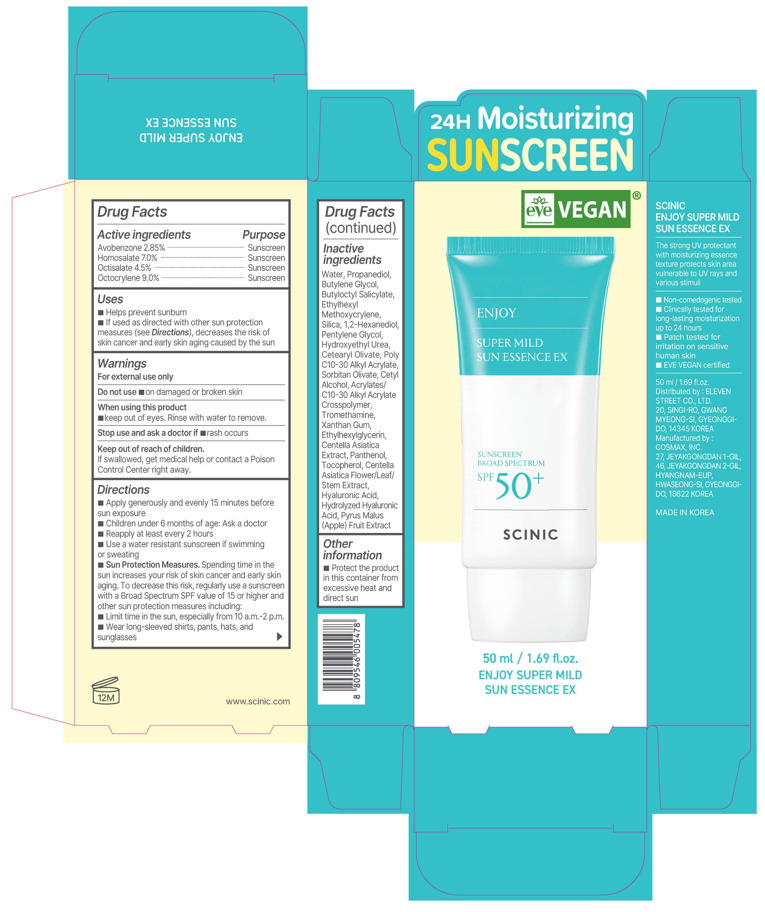 DRUG LABEL: SCINIC ENJOY SUPER MILD SUN ESSENCE EX
NDC: 85637-2505 | Form: LOTION
Manufacturer: ELEVEN STREET
Category: otc | Type: HUMAN OTC DRUG LABEL
Date: 20251222

ACTIVE INGREDIENTS: HOMOSALATE 7 g/100 mL; OCTOCRYLENE 9 g/100 mL; OCTISALATE 4.5 g/100 mL; AVOBENZONE 2.85 g/100 mL
INACTIVE INGREDIENTS: CETYL ALCOHOL; ETHYLHEXYL METHOXYCRYLENE; WATER; SORBITAN OLIVATE; PYRUS MALUS (APPLE) FRUIT; BUTYLOCTYL SALICYLATE; 1,2-HEXANEDIOL; BUTYLENE GLYCOL; PROPANEDIOL; TROMETHAMINE; CENTELLA ASIATICA FLOWERING TOP; HYALURONIC ACID; HYDROXYETHYL UREA; PANTHENOL; CETEARYL OLIVATE; XANTHAN GUM; ETHYLHEXYLGLYCERIN; CENTELLA ASIATICA TRITERPENOIDS; TOCOPHEROL; PENTYLENE GLYCOL; BEHENYL ACRYLATE POLYMER; SILICA

Warnings

For external use only

Do not use ■ on damaged or broken skin

When using this product
■ keep out of eyes. Rinse with water to remove.

Stop use and ask a doctor if ■ rash occurs

Keep out of reach of children.
If swallowed, get medical help or contact a Poison Control Center right away.

Directions

■ Apply generously and evenly 15 minutes before sun exposure
■ Children under 6 months of age: Ask a doctor
■ Reapply at least every 2 hours
■ Use a water resistant sunscreen if swimming or sweating

Sun Protection Measures. Spending time in the sun increases your risk of skin cancer and early skin aging. To decrease this risk, regularly use a sunscreen with a Broad Spectrum SPF value of 15 or higher and other sun protection measures including:
■ Limit time in the sun, especially from 10 a.m.–2 p.m.
■ Wear long-sleeved shirts, pants, hats, and sunglasses

Inactive ingredients

Water, Propanediol, Butylene Glycol, Butyloctyl Salicylate, Ethylhexyl Methoxycinnamate, Silica, 1,2-Hexanediol, Pentylene Glycol, Hydroxyethyl Urea, Cetearyl Olivate, Poly C10-30 Alkyl Acrylate, Sorbitan Olivate, Cetyl Alcohol, Acrylates/C10-30 Alkyl Acrylate Crosspolymer, Tromethamine, Xanthan Gum, Ethylhexylglycerin, Centella Asiatica Extract, Panthenol, Tocopherol, Centella Asiatica Flower/Leaf/Stem Extract, Hyaluronic Acid, Hydrolyzed Hyaluronic Acid, Pyrus Malus (Apple) Fruit Extract

Uses

■ Helps prevent sunburn
■ If used as directed with other sun protection measures (see Directions), decreases the risk of skin cancer and early skin aging caused by the sun

KEEP OUT OF REACH OF CHILDREN

If swallowed, get medical help or contact a Poison Control Center right away.

Purpose

Sunscreen